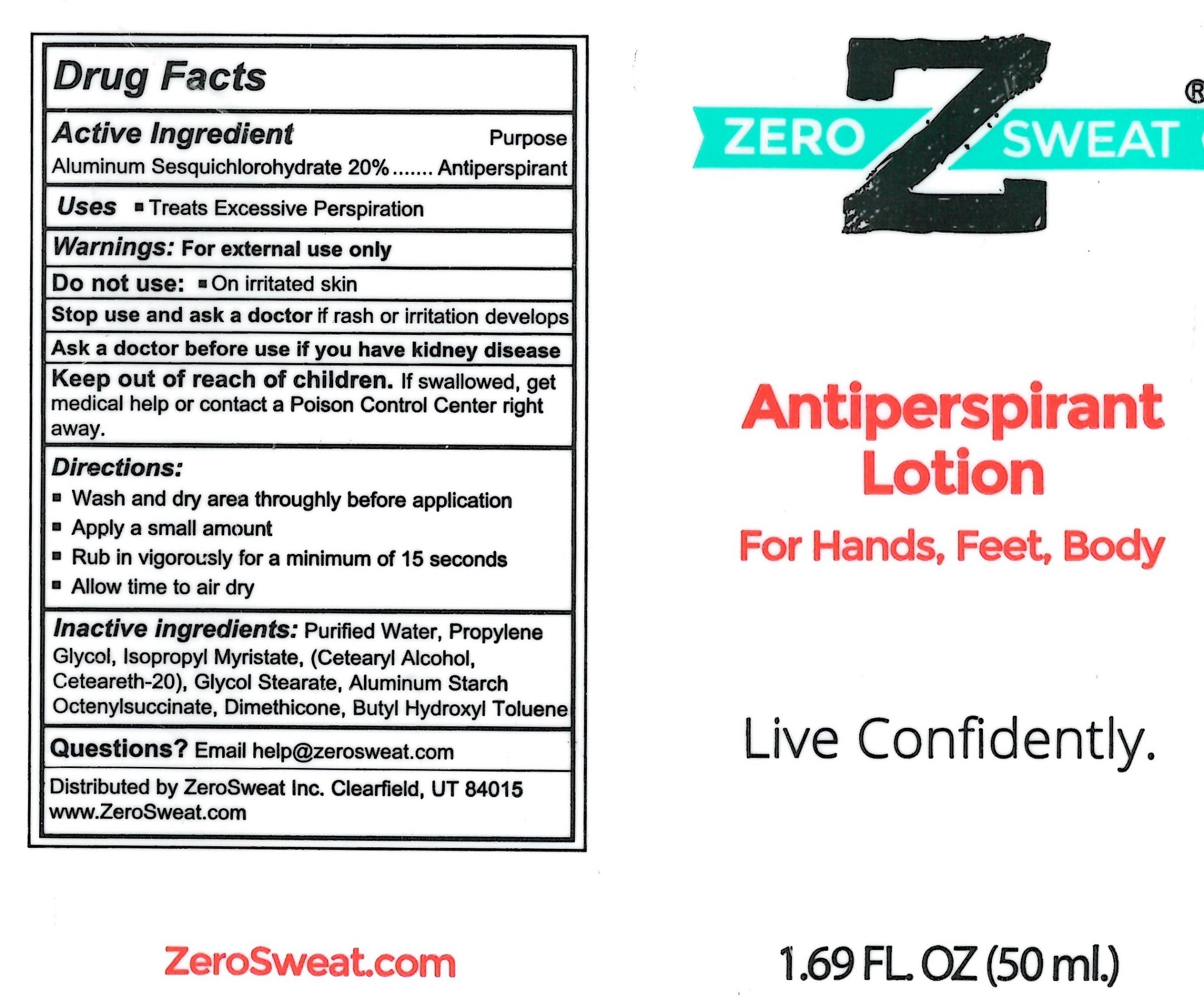 DRUG LABEL: Zero Sweat
NDC: 65112-267 | Form: LOTION
Manufacturer: I Shay Cosmetics Inc.
Category: otc | Type: HUMAN OTC DRUG LABEL
Date: 20210623

ACTIVE INGREDIENTS: ALUMINUM SESQUICHLOROHYDRATE 0.2 g/1 g
INACTIVE INGREDIENTS: GLYCOL STEARATE 0.04 g/1 g; PROPYLENE GLYCOL 0.04 g/1 g; ISOPROPYL MYRISTATE 0.04 g/1 g; WATER 0.27 g/1 g

Zero sweat 20% Lotion

dosage & administration

Directions

wash and dry area thoroughly before application

apply a small amount

rub in vigorously for a minimum of 15 seconds

allow time to dry

inactive ingredients

water

propylene glycol

isopropyl myristate

glycol stearate

cetearyl alcohol

polysorbate 60

aluminum starch octenlysuccinate

dmethicone

butyl hydroxyl toluene

indications and usage

Uses

treats excessive perspiration

active ingredient

aluminum sesquichlorohydrate

keep out of reach of children

if swallowed, get medical help or contact a poison control center right away

purpose

antiperspirant

warnings

for externasl use only

do not use on irritated skin

stop use and ask doctor is rash or irritation develops

ask a doctor before use if you have kidney disease